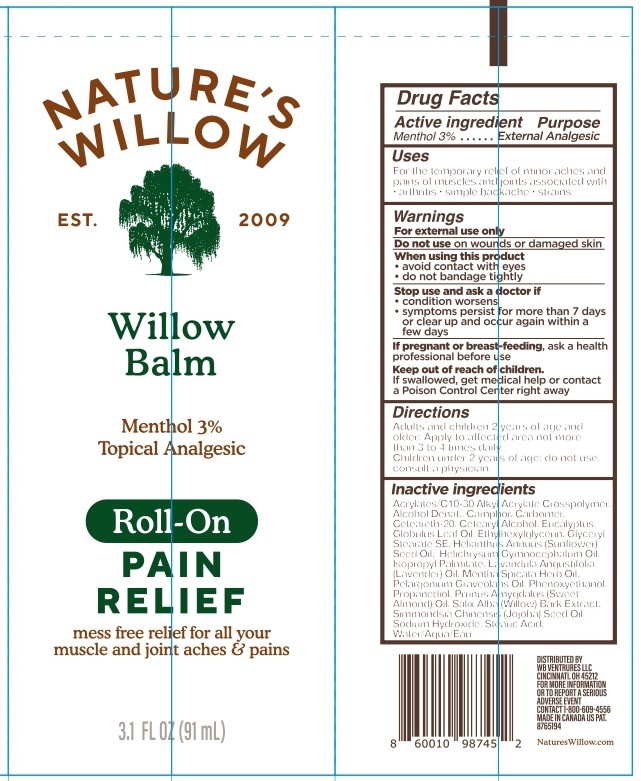 DRUG LABEL: Natures Willow Balm Roll On Pain Relief
NDC: 73498-029 | Form: LIQUID
Manufacturer: WB Ventures LLC
Category: otc | Type: HUMAN OTC DRUG LABEL
Date: 20250729

ACTIVE INGREDIENTS: MENTHOL 30 mg/1 mL
INACTIVE INGREDIENTS: PRUNUS AMYGDALUS DULCIS (SWEET ALMOND) OIL; STEARIC ACID; GLYCERYL STEARATE SE; PHENOXYETHANOL; HELIANTHUS ANNUUS (SUNFLOWER) SEED OIL; SALIX ALBA WHOLE; ALCOHOL; CETEARETH-20; WATER; ACRYLATES/C10-30 ALKYL ACRYLATE CROSSPOLYMER (60000 MPA.S AT 0.5%); SIMMONDSIA CHINENSIS (JOJOBA) SEED OIL; CAMPHOR (NATURAL); CARBOMER; ISOPROPYL PALMITATE; HELICHRYSUM GYMNOCEPHALUM WHOLE; PELARGONIUM GRAVEOLENS FLOWER OIL; SODIUM HYDROXIDE; CETEARYL ALCOHOL; ETHYLHEXYLGLYCERIN; LAVANDULA ANGUSTIFOLIA (LAVENDER) OIL; EUCALYPTUS GLOBULUS LEAF OIL

Nature's Willow Balm Roll On Pain Relief

Active Ingredient

Menthol 3%

Purpose

External Analgesic

Uses

For the temporary relief of minor aches and pains of muscles and joints associated with

- arthritis
- simple backache
- strains

Warnings

For external use only

Do not use on wounds or damaged skin

When using this product

avoid contact with eyes
do not bandage tightly

Stop use and ask a doctor if

conditions worsen
symptoms persist for more than 7 days or clear up and occur again within a few days

If pregnant or breast-feeding, ask a health professional before use

Keep out of reach of children. If swallowed, get medical help or contact a Poison Control Center right away

Directions

Adults and children 2 years of age and older: Apply to affected area not more than 3 to 4 times daily.

Children under 2 years of age: do not use, consult a physician.

Inactive Ingredients

Acrylates/C10-30 Alkyl Acrylate Crosspolymer, Alcohol Denat., Camphor, Carbomer, Ceteareth-20, Cetearyl Alcohol, Eucalyptus Globulus Leaf Oil, Ethylhexylglycerin, Glyceryl Stearate SE, Helianthus Annuus (Sunflower) Seed Oil, Helichrysum Gymnocephalum Oil, Isopropyl Palmitate, Lavandula Angustifolia (Lavender) Oil, Mentha Spicata Herb Oil, Pelargonium Graveolans Oil, Phenoxyethanol, Propanediol, Prunus Amygdalus (Sweet Almond) Oil, Salix Alba (Willow) Bark Extract, Simmondsia Chinensis (Jojoba) Seed Oil, Sodium Hydroxide, Stearic Acid, Water/Aqua/Eau

Distributed by WB Ventures LLC, Cincinnati, OH 45212

For more information or to report a serious adverse event contact 1-888-609-4556